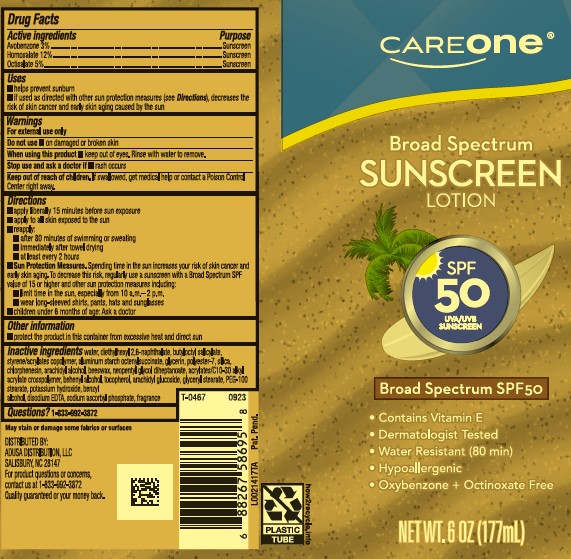 DRUG LABEL: Sunscreen
NDC: 72476-951 | Form: LOTION
Manufacturer: Retail Business Services, LLC 
Category: otc | Type: HUMAN OTC DRUG LABEL
Date: 20260206

ACTIVE INGREDIENTS: AVOBENZONE 30 mg/1 mL; HOMOSALATE 120 mg/1 mL; OCTISALATE 50 mg/1 mL
INACTIVE INGREDIENTS: WATER; DIETHYLHEXYL 2,6-NAPHTHALATE; BUTYLOCTYL SALICYLATE; BUTYL ACRYLATE/METHYL METHACRYLATE/METHACRYLIC ACID COPOLYMER (18000 MW); ALUMINUM STARCH OCTENYLSUCCINATE; GLYCERIN; POLYESTER-7; SILICON DIOXIDE; CHLORPHENESIN; ARACHIDYL ALCOHOL; YELLOW WAX; NEOPENTYL GLYCOL DIHEPTANOATE; ACRYLATES/C10-30 ALKYL ACRYLATE CROSSPOLYMER (60000 MPA.S); DOCOSANOL; TOCOPHEROL; ARACHIDYL GLUCOSIDE; GLYCERYL MONOSTEARATE; PEG-100 STEARATE; POTASSIUM HYDROXIDE; BENZYL ALCOHOL; EDETATE DISODIUM ANHYDROUS; SODIUM ASCORBYL PHOSPHATE

Care One D50.000/D50AA
Moisturizing Sunscreen Lotion SPF 50

Active ingredients

Avobenzone 3%

Homosalate 12%

Octisalate 5%

Purpose

Sunscreen

Uses

- helps prevent sunburn
- if used as directed with other sun protection measures (see Directions), decreases the risk of skin cancer and early skin aging caused by the sun

Warnings

For external use only

Do not use

- on damaged or broken skin

When using this product

- keep out of eyes. Rinse with water to remove.

Stop use and ask a doctor if

- rash occurs

Keep out of reach of children.

If swallowed, get medical help or contact a Poison Control Center right away.

Directions

- apply liberaly 15 minutes before sun exposure
- apply to all skin exposed to the sun
- reapply:
- after 80 minutes of swimming or sweating
- immediately after towel drying
- at least every 2 hours
- Sun Protection Measures. Spending time in the sun increases your risk of skin cancer and early skin aging. To decrease this risk, regularly use a sunscreen with Broad Spectrum SPF value of 15 or higher and other sun protection measures including:
- limit time in the sun, especially from 10 a.m. -2 p.m.
- wear long-sleeved shirts, pants, hats and sunglasses
- children under 6 months of age: Ask a doctor

Other information

- protect the product in this container from excessive heat and direct sun

Inactive ingredients

water, diethylhexyl 2,6-naphthalate, butyloctyl salicylate, styrene/acrylates copolymer, aluminum starch octenylsuccinate, glycerin, polyester-7, silica, chlorphenesin, arachidyl alcohol, beeswax, neopentyl glycol diheptanoate, acrylates/C10-30 alkyl acrylate crosspolymer, behenyl alcohol, tocopherol, arachidyl glucoside, glyceryl stearate, PEG-100 stearate, potassium hydroxide, benzyl alcohol, disodium EDTA, sodium ascorbyl phosphate, fragrance

ADVERSE REACTION

May stain or damage some fabrics or surfaces

DISTRIBUTED BY:

ADUSA DISTRIBUTION, LLC

SALISBURY, NC 28147

For product questions or concerns, contact us at 1-833-992-3872

Quality guaranteed or your money back.

Pat. Pend.

principal display panel

CAREONE®

Broad Spectrum

SUNSCREEN LOTION

SPF 50

UVA/UVB SUNSCREEN

Broad Spectrum SPF 50

- Contains Vitamin E
- Dermatologist tested
- Water resistant (80 minutes)
- Hypoallergenic
- Oxybenzone + Octinoxate Free

NET WT. 6 FL OZ (177 mL)